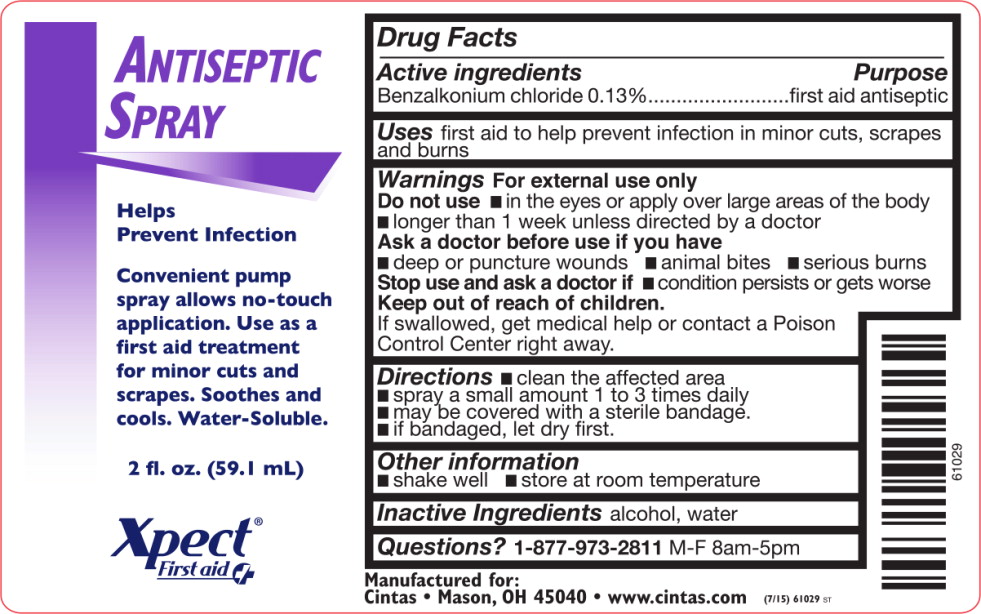 DRUG LABEL: Antiseptic
NDC: 68421-7120 | Form: LIQUID
Manufacturer: Cintas First Aid & Safety
Category: otc | Type: HUMAN OTC DRUG LABEL
Date: 20130604

ACTIVE INGREDIENTS: benzalkonium chloride 1.2478 g/1 L
INACTIVE INGREDIENTS: alcohol; water

Drug Facts

Active Ingredient

Benzalkonium Chloride 0.13%

Purpose

First aid antiseptic

Uses

First aid to help prevent infection in minor cuts, scrapes and burns

Warnings

for external use only

Do not use

- in the eyes, or apply over large areas of the body
- longer than 1 week unless directed by a doctor

Ask a doctor before use if you have

- deep or puncture wounds, animal bites or serious burns

Stop use and ask a doctor if

- condition persists or gets worse

Keep out of reach of children. If swallowed, get medical help or contact a Poison Control Center right away

Directions

- clean the affected area
- spray a small amount of this product on the area 1 to 3 times daily
- may be covered with a sterile bandage
- if bandaged, let dry first

Other information

- shake well
- store at room temperature

Inactive ingredients

purified water, alcohol

STORAGE AND HANDLING

Store at room temperature

Questions or comments?

1-877-973-2811

Manufactured for: Cintas First Aid & Safety
Mason, OH 45040
Rev 04/13
#61029

PRINCIPAL DISPLAY PANEL – bottle label

Antiseptic
Spray
Helps
Prevent Infection

Convenient pump
spray allows no-touch
application. Use as a
first aid treatment for
minor cuts and scrapes.
Soothes and cools.
Water-Soluble.

2 fl. oz. (59.1 mL)

Xpect
First Aid